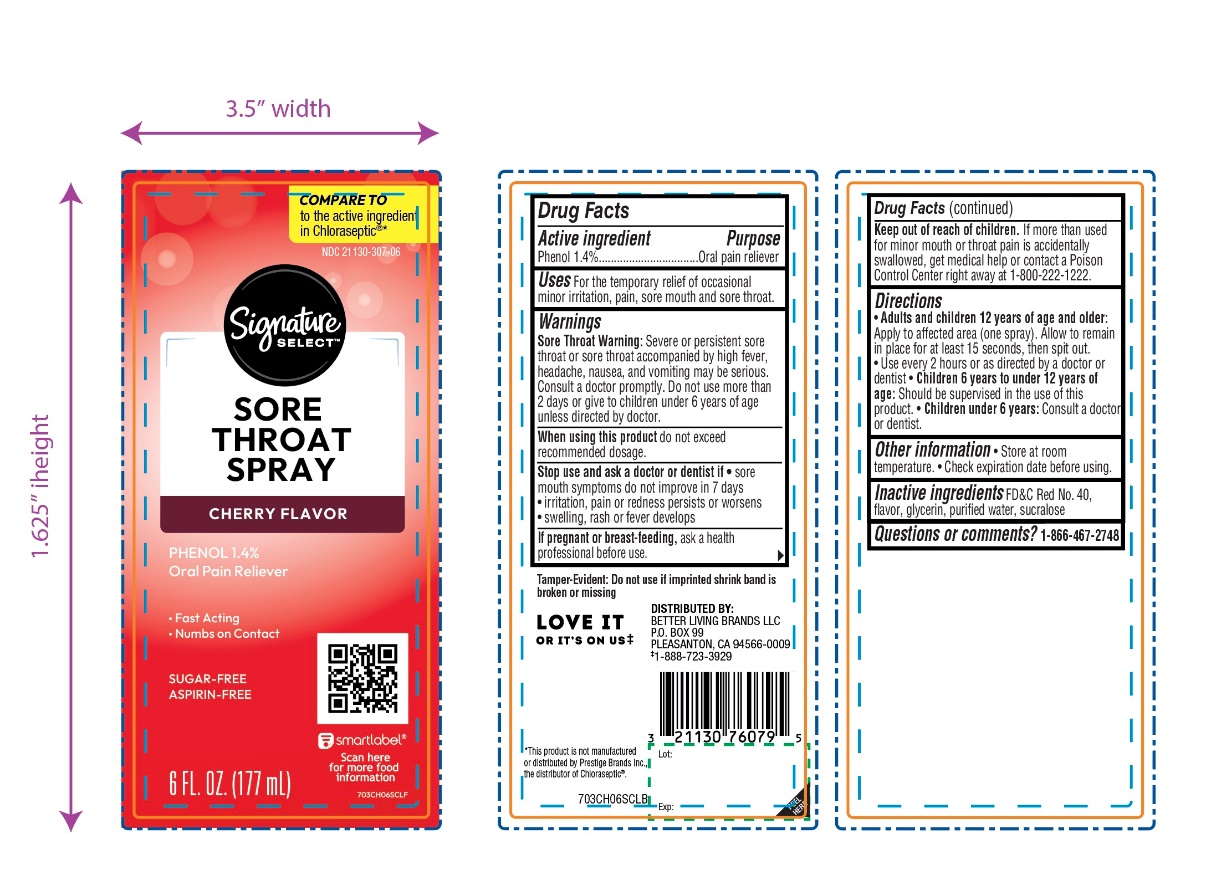 DRUG LABEL: SIGNATURE CARE
NDC: 21130-196 | Form: SPRAY
Manufacturer: SAFEWAY
Category: otc | Type: HUMAN OTC DRUG LABEL
Date: 20260223

ACTIVE INGREDIENTS: PHENOL 1.4 g/100 mL
INACTIVE INGREDIENTS: FD&C RED NO. 40; GLYCERIN; WATER; SUCRALOSE

Signature SELECT Sore Throat Spray Cherry Flavor

Active ingredient

Phenol 1.4%

Purpose

Oral pain reliever

Uses

for the temporarily relief of occasional minor irritation, pain, sore mouth, and sore throat.

Warnings

Sore throat warning: Severe or persistent sore throat or sore throat accompanied by high fever, headache, nausea, and vomiting may be serious. Consult a doctor promptly. Do not use more than 2 days or give to children under 6 years of age unless directed by a doctor.

When using this product,

do not exceed recommended dosage.

Stop use and ask a dentist or doctor if

- sore mouth symptoms do not improve in 7 days
- irritation, pain or redness persists or worsens
- swelling, rash or fever develops

If pregnant or breast-feeding,

ask a heath professional before use.

Keep out of reach of children.

If more than used for minor mouth or throat pain is accidentally swallowed, get medical help or contact a Poison Control Center right away at 1-800-222-1222

Directions

- Adults and children 12 years of age and older: Apply to affected area (one spray). Allow to remain in place for at least 15 seconds, then spit out
- Use every 2 hours as directed by a doctor or dentist
- Children 6 years to under 12 years of age: should be supervised in the use of this product
- Children under 6 years, Consult a doctor or dentist

Other information

- Store at room temperature.
- Check expiration date before using.

Inactive ingredients

FD&C Red #40, glycerin, flavor, purified water, sucralose.

Questions or comments?

1-866-467-2748

Principal Display Panel

Signature SELECT™

COMPARE TO the active ingredient in Chloraseptic®*

NDC# 21130-196-06

SORE THROAT SPRAY

CHERRY FLAVOR

Phenol 1.4%

Oral Pain Reliever

- Fast Acting
- Numbs on Contact

SUGAR-FREE

ASPIRIN-FREE

6 FL. OZ. (177 mL)

Tamper-Evident: Do not use if imprinted shrink band is broken or missing

Distributed by: BETTER LIVING BRANDS LLC

P.O. BOX 99

PLEASANTON, CA 94566-0009

‡1-888-723-3929

*This product is not manufactured or distributed by Prestige Brands, Inc., distributor of Chloraseptic®.